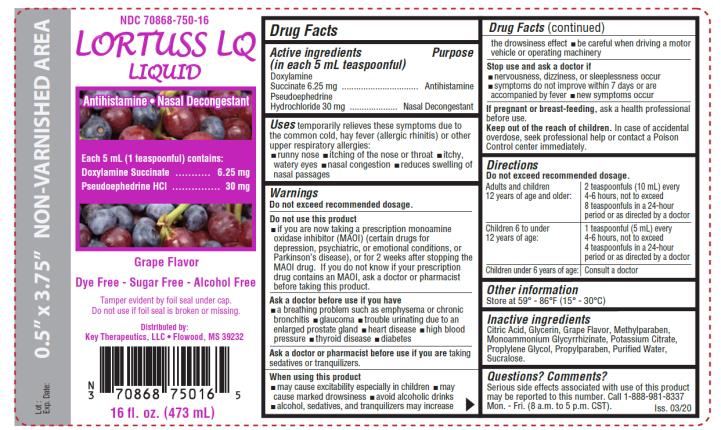 DRUG LABEL: LORTUSS LQ
NDC: 70868-750 | Form: LIQUID
Manufacturer: Key Therapeutics
Category: otc | Type: HUMAN OTC DRUG LABEL
Date: 20220126

ACTIVE INGREDIENTS: DOXYLAMINE SUCCINATE 6.25 mg/5 mL; PSEUDOEPHEDRINE HYDROCHLORIDE 30 mg/5 mL
INACTIVE INGREDIENTS: CITRIC ACID MONOHYDRATE; GLYCERIN; METHYLPARABEN; AMMONIUM GLYCYRRHIZATE; POTASSIUM CITRATE; POTASSIUM SORBATE; PROPYLPARABEN; PROPYLENE GLYCOL; WATER; SUCRALOSE

Lortuss LQ

LORTUSS LQ- doxylamine succinate, pseudoephedrine hydrochloride liquid

Key Therapeutics

Disclaimer: Most OTC drugs are not reviewed and approved by FDA; however, they may be marketed if they comply with applicable regulations and policies. FDA has not evaluated whether this product complies.

----------

LORTUSS LQ LIQUID

Drug Facts

Active ingredients

(in each 5 mL teaspoonful) Doxylamine Succinate 6.25 mg Pseudoephedrine Hydrochloride 30 mg

Purpose

Antihistamine Decongestant

Uses

temporarily relieves these symptoms due to the common cold, hay fever (allergic rhinitis) or other upper respiratory allergies:

- runny nose
- itching of the nose or throat itchy, watery eyes
- nasal congestion
- reduces swelling of nasal passage

Warnings

Do not exceed recommended dosage.

Do not use this product

- if you are now taking a prescription monoamine oxidase inhibitor (MAOI) (certain drugs for depression, psychiatric, or emotional conditions, or Parkinson's disease), or for 2 weeks after stopping the MAOI drug. If you do not know if your prescription drug contains an MAOI, ask a doctor or pharmacist before taking this product.

Ask a doctor before use if you have

a breathing problem such as emphysema or chronic bronchitis especially in children glaucoma

trouble urinating due to an enlarged prostate gland heart disease

high blood pressure thyroid disease diabetes mellitus

Ask a doctor or pharmacist before use if you are

now taking sedatives or tranquilizers.

When using this product

- may cause excitability especially in children
- may cause marked drowsiness
- avoid alcoholic drinks
- alcohol, sedatives, and tranquilizers may increase the drowsiness effect
- be careful when driving a motor vehicle or operating machinery

Stop use and ask a doctor if

- nervousness, dizziness, or sleeplessness occur
- symptoms do not improve within 7 days or are accompanies by fever
- new symptoms occur

If pregnant or breast-feeding,

ask a health professional before use.

Keep out of the reach of children.

In case of accidental overdose seek professional help or contact a Poison Control Center immediately.

Directions

Do not exceed recommended dosage.

Adults and children 12 years of age and older: | 2 teaspoonfuls (10 mL) every 6 hours, not to exceed 8 teaspoonfuls in 24-hour period or as directed by a doctor.
Children 6 to under 12 years of age: | 1 teaspoonful (5 mL) every 6 hours, not to exceed 4 teaspoonfuls in a 24-hour period or as directed by a doctor.
Children under 6 years of age: | Consult a doctor

Other information

Store at 59° - 86°F (15° - 30°C)

Inactive ingredients

Citric Acid, Glycerin, Grape Flavor, Methylparaben, Monoammonium Glycyrrhizinate, Potassium Citrate, Potassium Sorbate, Propylparaben, Propylene Glycol, Purified Water, Sucralose.

Questions? Comments?

Serious side effects associated with use of this product May be reported to this number. Call 1-888-981-8337

Mon - Fri (8 a.m. to 5 p.m. CST)

Principal Display Panel

NDC 70868-750-16 LORTUSS LQ

Antihistamine / Decongestant

Each 5 mL (1 teaspoonful) contains: Doxylamine Succinate……………6.25 mg

Pseudoephedrine HCl……………30 mg

Grape Flavor

Dye Free - Sugar Free - Alcohol Free

16 fl oz. (473 mL)

Distributed by:

Key Therapeutics, LLC

Flowood, MS 39232

Iss. 03/20